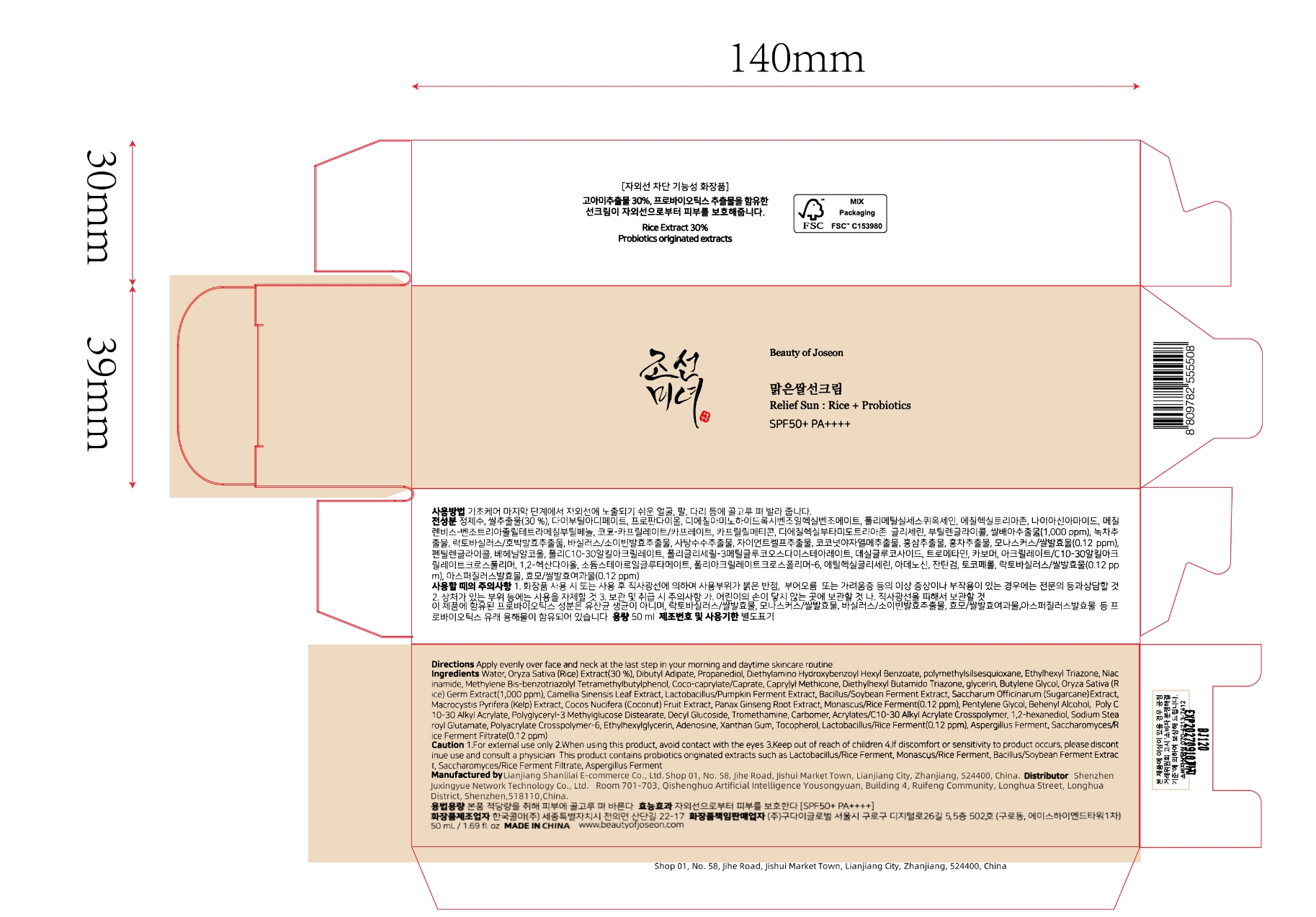 DRUG LABEL: Rice Probiotics
NDC: 85038-006 | Form: LOTION
Manufacturer: Lianjiang Shanlilai E-commerce Co., Ltd.
Category: otc | Type: HUMAN OTC DRUG LABEL
Date: 20250115

ACTIVE INGREDIENTS: RICE GERM 0.3 g/1 mL
INACTIVE INGREDIENTS: PROPANEDIOL; DIETHYLAMINO HYDROXYBENZOYL HEXYL BENZOATE; DIBUTYL ADIPATE

Rice Probiotics

ACTIVE INGREDIENT

Oryza Sativa (Rice) Extract 30%

PURPOSE

sunscreen cream

KEEP OUT OF REACH OF CHILDREN SECTION

INDICATIONS AND USAGE

sunscreen cream

WARNINGS

1.For external use only 2.when using this product, avoid contact with the eyes

DOSAGE AND ADMINISTRATION

Apply evenly over face and neck at the last step in ycur morning and daytime skincare routine

INACTIVE INGREDIENT

Dibutyl Adipate
Propanediol
Diethylamino Hydroxybenzoyl
Hexyl Benzoate